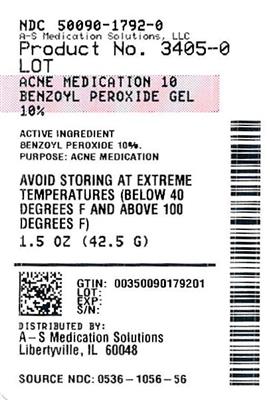 DRUG LABEL: Rugby Benzoyl Peroxide 
NDC: 50090-1792 | Form: GEL
Manufacturer: A-S Medication Solutions
Category: otc | Type: HUMAN OTC DRUG LABEL
Date: 20241106

ACTIVE INGREDIENTS: BENZOYL PEROXIDE 100 mg/1 mL
INACTIVE INGREDIENTS: CELLULOSE GUM; Edetate Disodium; Laureth-4; Sodium Hydroxide; CI 77891; Water

Rugby® 10% Benzoyl Peroxide Gel

Drug Facts

Active ingredient

Benzoyl peroxide USP 10%

Purpose

Acne medication

Use

for the treatment of acne

Warnings

For external use only.

Do not use if you

- have very sensitive
- are sensitive to benzoyl peroxide

When using this product

- avoid unnecessary sun exposure and use a sunscreen
- avoid contact with eyes, lips and mouth
- avoid contact with hair or dyed fabrics, which may be bleached by this product
- skin irritation may occur, characterized by redness, burning, itching, peeling, or possibly swelling. Irritation may be reduced by using the product less frequently or in a lower concentration.
- skin irritation and dryness is more likely to occur if you use another topical acne medication at the same time. If irritation occurs, only use one topical acne medication at a time.

Stop use and consult a doctor if

- irritation becomes severe

PREGNANCY OR BREAST FEEDING

If pregnant or breast-feeding, ask a health professional before use.

Keep out of reach of children. If swallowed, get medical help or contact a Poison Control Center (1-800-222-1222) immediately.

Directions

- clean the skin thoroughly before applying this product
- cover the entire affected area with a thin layer one to three times daily
- because excessive drying of the skin may occur, start with one application daily, then gradually increase to two or three times daily if needed or as directed by a doctor
- if bothersome dryness or peeling occurs, reduce application to once a day or every other day
- if going outside, apply sunscreen after using this product
- if irritation or sensitivity develops, stop use of both products and ask a doctor.

Other information

- keep tightly closed
- store at room temperature

Inactive ingredients

carbomer, disodium EDTA, hydroxypropyl methylcellulose, laureth-4, sodium hydroxide, water

Questions or comments?

1-800-645-2158

Distributed by:
RUGBY® LABORATORIES
17177 N Laurel Park Drive, Suite 233
Livonia, MI 48152

HOW SUPPLIED

Product: 50090-1792

NDC: 50090-1792-0 42.5 mL in a TUBE / 1 in a CARTON